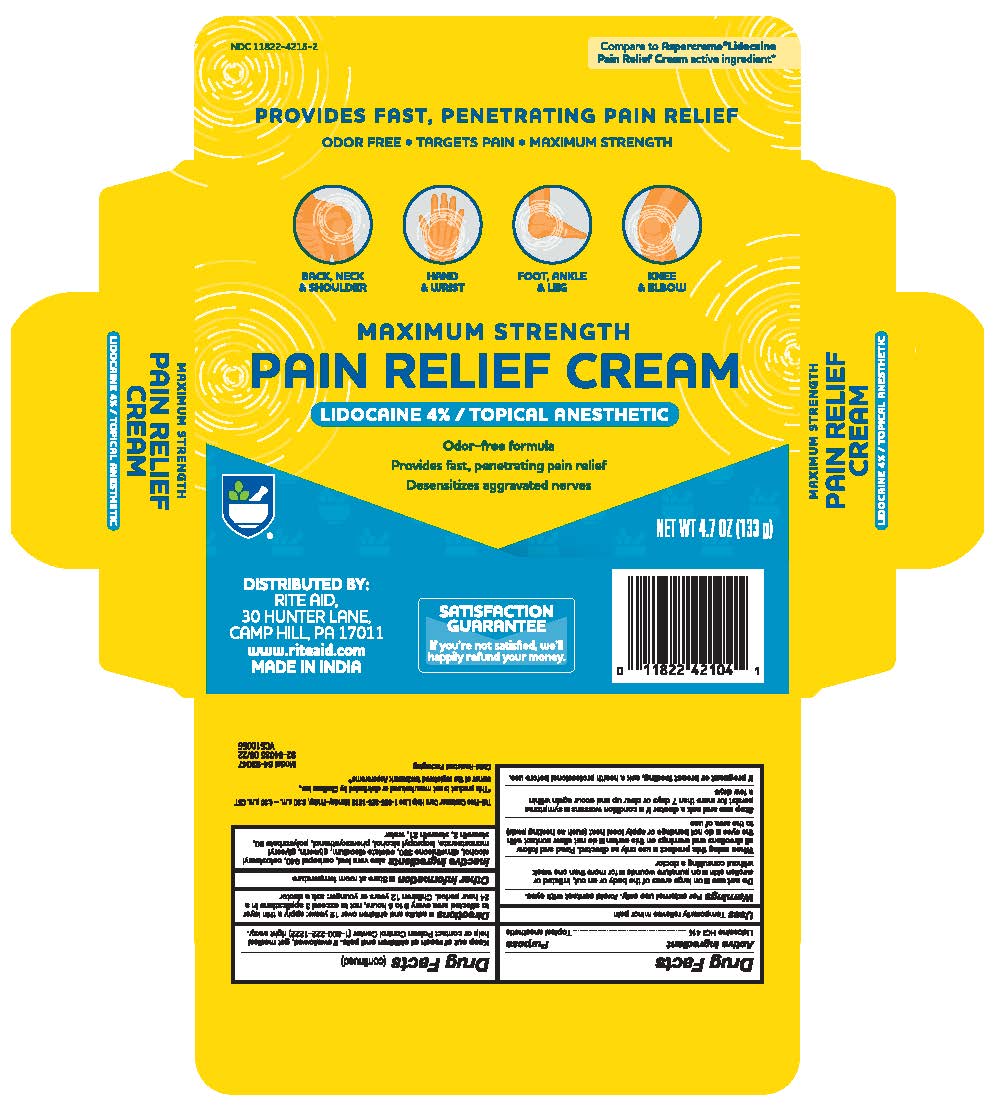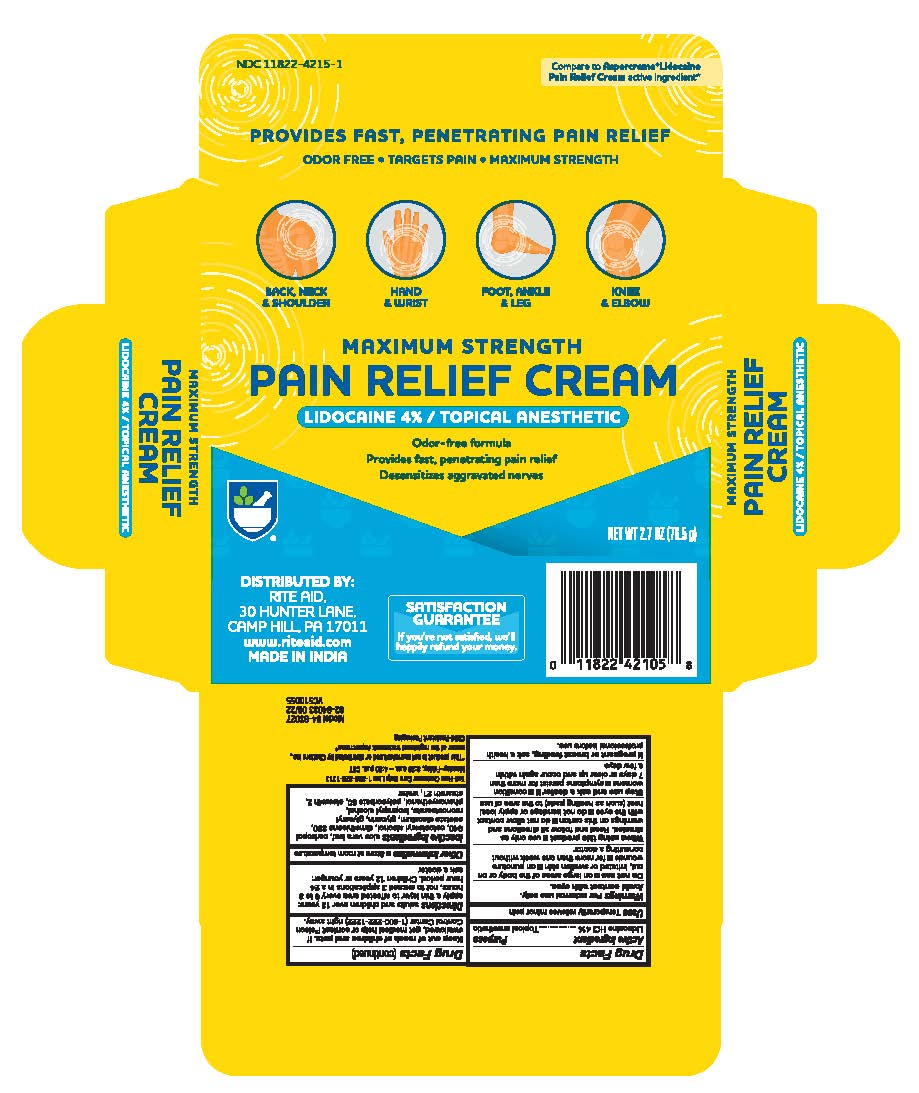 DRUG LABEL: Rite Aid Pain Relief Cream with Lidocaine
NDC: 11822-4215 | Form: CREAM
Manufacturer: Rite Aid
Category: otc | Type: HUMAN OTC DRUG LABEL
Date: 20241218

ACTIVE INGREDIENTS: LIDOCAINE HYDROCHLORIDE 4 g/100 g
INACTIVE INGREDIENTS: CARBOMER 940; ALOE VERA LEAF; STEARETH-2; GLYCERIN; CETOSTEARYL ALCOHOL; ISOPROPYL ALCOHOL; PHENOXYETHANOL; DIMETHICONE 350; EDETATE DISODIUM; POLYSORBATE 60; GLYCERYL MONOSTEARATE; STEARETH-21; WATER

Rite Aid Pain Relief cream with Lidocaine

Drug Facts

Active ingredient

Lidocaine HCI 4%

Purpose

Topical anesthetic

Uses

temporarily relieves minor pain

Warnings

For external use only. Avoid contact with eyes

Do not use

- on large areas of the body or on cut, irritated or swollen skin
- on puncture wounds
- for more than one week without consulting a doctor

When using this product

- use only as directed. Read and follow all directions and warnings on this carton.
- do not allow contact with the eyes
- do not bandage or apply local heat (such as heating pads) to the area of use

Stop use and ask a doctor if

- condition worsens
- symptoms persist for more than 7 days or clear up and occur again within a few days

If pregnant or breast-feeding,

ask a health professional before use.

Keep out of reach of children and pets.

If swallowed, get medical help or contact a Poison Control Center (1-800-222-1222) right away.

Directions

adults and children over 12 years:

- apply a thin layer to affected area every 6 to 8 hours, not to exceed 3 applications in a 24 hour period

children 12 years and younger: ask a doctor

Other Information

Store at room temperature

Inactive ingredients

aloe vera leaf, carbopol 940, cetostearyl alcohol, dimethicone 350, edetate disodium, glycerin, glyceryl monostearate, isopropyl alcohol, phenoxyethanol, polysorbate 60, steareth 2, steareth 21, water